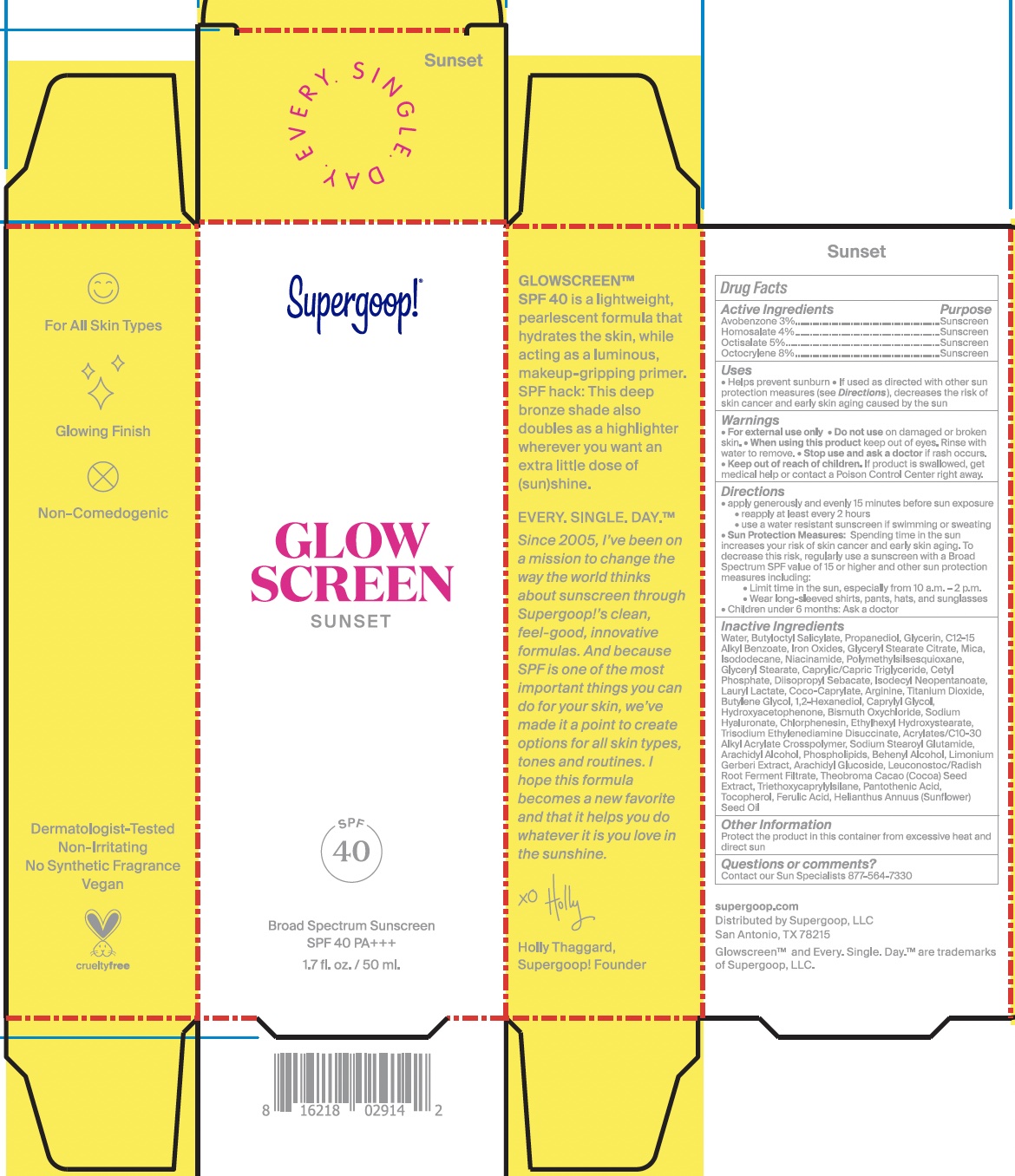 DRUG LABEL: Glowscreen SPF 40 -Sunset
NDC: 75936-608 | Form: LOTION
Manufacturer: Supergoop, LLC
Category: otc | Type: HUMAN OTC DRUG LABEL
Date: 20241205

ACTIVE INGREDIENTS: OCTISALATE 5 g/100 mL; OCTOCRYLENE 8 g/100 mL; HOMOSALATE 4 g/100 mL; AVOBENZONE 3 g/100 mL
INACTIVE INGREDIENTS: 1,2-HEXANEDIOL; BUTYLOCTYL SALICYLATE; PROPANEDIOL; LAURYL LACTATE; GLYCERYL MONOSTEARATE; CETYL PHOSPHATE; HYDROXYACETOPHENONE; FERULIC ACID; ALKYL (C12-15) BENZOATE; ISODODECANE; MEDIUM-CHAIN TRIGLYCERIDES; COCO-CAPRYLATE; ISODECYL NEOPENTANOATE; ARACHIDYL ALCOHOL; DOCOSANOL; LIMONIUM PLATYPHYLLUM WHOLE; ARACHIDYL GLUCOSIDE; LEUCONOSTOC/RADISH ROOT FERMENT FILTRATE; COCOA; SUNFLOWER OIL; ARGININE; POLYMETHYLSILSESQUIOXANE (4.5 MICRONS); TITANIUM DIOXIDE; BUTYLENE GLYCOL; TRIETHOXYCAPRYLYLSILANE; PANTOTHENIC ACID; TOCOPHEROL; CAPRYLYL GLYCOL; OMEGA-3 FATTY ACIDS; HYALURONATE SODIUM; ETHYLHEXYL HYDROXYSTEARATE; CARBOMER COPOLYMER TYPE A (ALLYL PENTAERYTHRITOL CROSSLINKED); SODIUM STEAROYL GLUTAMATE; BROWN IRON OXIDE; WATER O-18; GLYCERIN; GLYCERYL STEARATE CITRATE; DIISOPROPYL SEBACATE; MICA; NIACINAMIDE; TRISODIUM ETHYLENEDIAMINE DISUCCINATE; BISMUTH OXYCHLORIDE; CHLORPHENESIN

Glowscreen SPF 40 Sunset

Active Ingredients:

Avobenzone 3%, Homosalate 4%, Octisalate 5%, Octocrylene 8%

Uses:

Helps prevent sunburn • If used as directed with other sun protection measures (see Directions), decreases the risk of skin cancer and early skin aging caused by the sun

WARNINGS

For external use only • Do not use on damaged or broken skin • Stop use and ask a doctor if rash occurs • When using this product keep out of eyes • Rinse with water to remove

• Keep out of reach of children • If swallowed, get medical help or contact a Poison Control Center right away

• Stop use and ask a doctor if rash occurs

Directions:

apply generously and evenly 15 minutes before sun exposure • reapply at least every 2 hours • use a water resistant sunscreen if swimming or sweating • Sun Protection Measures. Spending time in the sun increases your risk of skin cancer and early skin aging. To decrease this risk, regularly use a sunscreen with broad spectrum SPF of 15 or higher and other sun protection measures including: • limit time in the sun, especially from 10 a.m. - 2 p.m. • wear long-sleeve shirts, pants, hats, and sunglasses • Children under 6 months: Ask a doctor

STORAGE AND HANDLING

Protect the product in this container from excessive heat and direct sun

INACTIVE INGREDIENT

Water, Butyloctyl Salicylate, Propanediol, Glycerin, C12-15 Alkyl Benzoate, Iron Oxides, Glyceryl Stearate Citrate, Mica, Isododecane, Niacinamide, Polymethylsilsesquioxane, Glyceryl Stearate, Caprylic/Capric Triglyceride, Cetyl Phosphate, Diisopropyl Sebacate, Isodecyl Neopentanoate, Lauryl Lactate, Coco-Caprylate, Arginine, Titanium Dioxide, Butylene Glycol, 1,2-Hexanediol, Caprylyl Glycol, Hydroxyacetophenone, Bismuth Oxychloride, Sodium Hyaluronate, Chlorphenesin, Ethylhexyl Hydroxystearate, Trisodium Ethylenediamine Disuccinate, Acrylates/C10-30 Alkyl Acrylate Crosspolymer, Sodium Stearoyl Glutamate, Arachidyl Alcohol, Phospholipids, Behenyl Alcohol, Limonium Gerberi Extract, Arachidyl Glucoside, Leuconostoc/Radish Root Ferment Filtrate, Theobroma Cacao (Cocoa) Seed Extract, Triethoxycaprylylsilane, Pantothenic Acid, Tocopherol, Ferulic Acid, Helianthus Annuus (Sunflower) Seed Oil

PACKAGE LABEL

Supergoop!

Glow Screen SPF 40

Sunset

1.7 fl. oz./ 50 mL